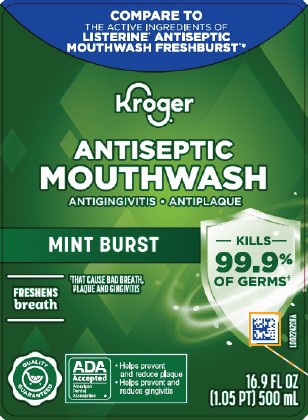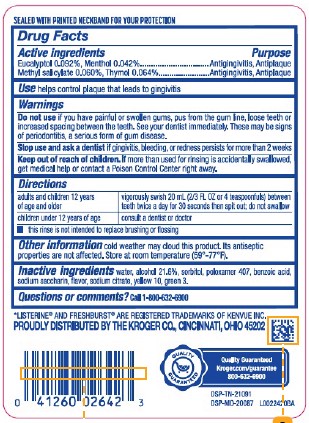 DRUG LABEL: Mouth Rinse
NDC: 30142-072 | Form: MOUTHWASH
Manufacturer: The Kroger Co.
Category: otc | Type: HUMAN OTC DRUG LABEL
Date: 20260227

ACTIVE INGREDIENTS: EUCALYPTOL 0.92 mg/1 mL; MENTHOL 0.42 mg/1 mL; METHYL SALICYLATE 0.6 mg/1 mL; THYMOL 0.64 mg/1 mL
INACTIVE INGREDIENTS: WATER; ALCOHOL; SORBITOL; POLOXAMER 407; BENZOIC ACID; SACCHARIN SODIUM; SODIUM CITRATE; D&C YELLOW NO. 10; FD&C GREEN NO. 3

Kroger 072.003/072AL rev2-AN
Spring Mint Antiseptic Mouthrinse

TEP

SEALED WITH PRINTED NECKBAND FOR YOUR PROTECTION

Active ingredients

Eucalyptol 0.092%

Menthol 0.042%

Methyl salicylate 0.060%

Thymol 0.064%

Purpose

Antigingivitis, Antiplaque

Use

helps control plaque that leads to gingivitis

Warnings

For this product

Do not use

If you have painful or swollen gums, pus from the gum line, loose teeth or increased spacing between the teeth. See your dentist immediately. These may be signs of periodontitis, a serious form of gum disease.

Stop use and ask a dentist if

gingivitis, bleeding, or redness persists for more than 2 weeks

Keep out of reach of children

If more than used for rinsing is accidentally swallowed, get medical help or contact a Poison Control Center right away.

Directions

adults and children 12 years of age and older - vigorously swish 20 mL (2/3 FL OZ or 4 teaspoonfuls) between teeth twice a day for 30 seconds then spit out; do not swallow

children under 12 years of age - consult a dentist or doctor

- this rinse is not intended to replace brushing or flossing

Other information

Cold weather may cloud this product. Its antiseptic properties are not affected. Store at room temperature (59⁰- 77⁰F).

Inactive ingredients

water, alcohol 21.6%, sorbitol, poloxamer 407, benzoic acid, sodium saccharin, flavor, sodium citrate, yellow 10, green 3

Questions or comments?

Call 1-800-632-6900

Disclaimer

*LISTERINE®AND FRESHBURSTARE REGISTERED TRADEMARKS OF KENVUE, INC.

Adverse Reactions

PROUDLY DISTRIBUTED BY THE KROGER CO.

CINCINNATI, OHIO 45202

QUALITY GUARANTEED

Kroger.com/guarantee

800-632-6900

DSP-TN-21091

DSP-MO-20087

Principal display panel

COMPARE TO THE ACTIVE INGREDIENTS OF LISTERINE® ANTISEPTIC MOUTHWASH FRESHBURST®*

Kroger®

ANTISEPTIC MOUTHWASH

ANTGINGIVITIS • ANTIPLAQUE

MINT BURST

KILLS 99.9% OF GERMS†

FRESHENS breath

† THAT CAUSE BAD BREATH, PLAQUE AND GINGIVITIS

QUALITY GUARANTEED

ADA Accepted

American Dental Association

- Helps prevent and reduce plaque
- Helps prevent and reduce gingivitis

16.9 FL OZ (1.05 PT) 500 mL